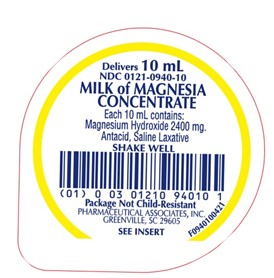 DRUG LABEL: Milk of Magnesia Concentrate
NDC: 0121-0940 | Form: SUSPENSION
Manufacturer: PAI Holdings, LLC dba PAI Pharma
Category: otc | Type: HUMAN OTC DRUG LABEL
Date: 20241112

ACTIVE INGREDIENTS: MAGNESIUM HYDROXIDE 2400 mg/10 mL
INACTIVE INGREDIENTS: HYPROMELLOSE, UNSPECIFIED; TRISODIUM CITRATE DIHYDRATE; PROPYLENE GLYCOL; METHYLPARABEN; PROPYLPARABEN; GLYCERIN; SORBITOL SOLUTION; SACCHARIN SODIUM; SUCROSE; WATER

MILK OF MAGNESIA CONCENTRATE

Drug Facts

Active ingredient (in each 10 mL)

Magnesium hydroxide 2400 mg

Purpose

Saline laxative

Uses

As an Antacid

- heartburn
- upset/sour stomach
- acid indigestion

As a Laxative

- relieves occasional constipation (irregularity) This product usually produces bowel movement in ½ to 6 hours.

Warnings

Do not use if you have ever had an allergic reaction to this product or any of its ingredients

Ask a doctor before use if you have

- kidney disease
- a magnesium-restricted diet
- stomach pain, nausea, or vomiting
- a sudden change in bowel habits that lasts over 14 days

Ask a doctor or pharmacist before use If you are taking a prescription drug. This product may interact with certain prescription drugs.

Stop use and ask a doctor if

- you have rectal bleeding or no bowel movement after using this product. These could be signs of a serious condition.
- you need to use a laxative for more than 1 week

PREGNANCY OR BREAST FEEDING

If pregnant or breast-feeding, ask a health professional before use.

Keep out of reach of children. In case of overdose, get medical help or contact a Poison Control Center right away.

Directions

As an Antacid

- do not exceed the maximum recommended daily dose of 20 mL in a 24 hour period
- shake well before use
- can be taken with water
- mL = milliliter

adults and children 12 years of age and over | 5 mL (1 teaspoonful)
children under 12 years of age | ask a doctor

As a Laxative

- do not exceed the maximum recommended daily dose in a 24 hour period
- shake well before use
- dose may be taken once a day preferably at bedtime, in divided doses, or as directed by a doctor. Drink a full glass (8 oz) of liquid with each dose.
- mL = milliliter

adults and children 12 years and older | 15 mL to 30 mL
children under 12 years | ask a doctor

Other information

- each teaspoonful (5 mL) contains: magnesium 1000 mg
- Sodium Content: 19 mg/10 mL
- store at room temperature, 20° - 25°C (68° - 77°F). Avoid freezing.
- Milk of Magnesia Concentrate (white suspension, lemon flavored) is supplied in the following oral dosage form:

NDC 0121-0940-10: 10 mL unit dose cup, in a tray of ten cups.

Inactive ingredients

glycerin, hydroxypropyl methylcellulose, lemon oil, methylparaben, propylene glycol, propylparaben, purified water, sodium citrate
dihydrate, sodium saccharin, sorbitol, and sucrose.

Questions or comments?

Call 1-800-845-8210

MANUFACTURED BY

Pharmaceutical
Associates, Inc.
Greenville, SC 29605
www.paipharma.com

R07/21

PRINCIPAL DISPLAY PANEL - 10 mL Unit-Dose Cup Tray Label

NDC 0121-0940-10

Milk of Magnesia Concentrate

Each 10 mL contains:

Magnesium Hydroxide 2400 mg.

ANTACID/ SALINE LAXATIVE

SHAKE WELL

Package Not Child-Resistant

See Insert